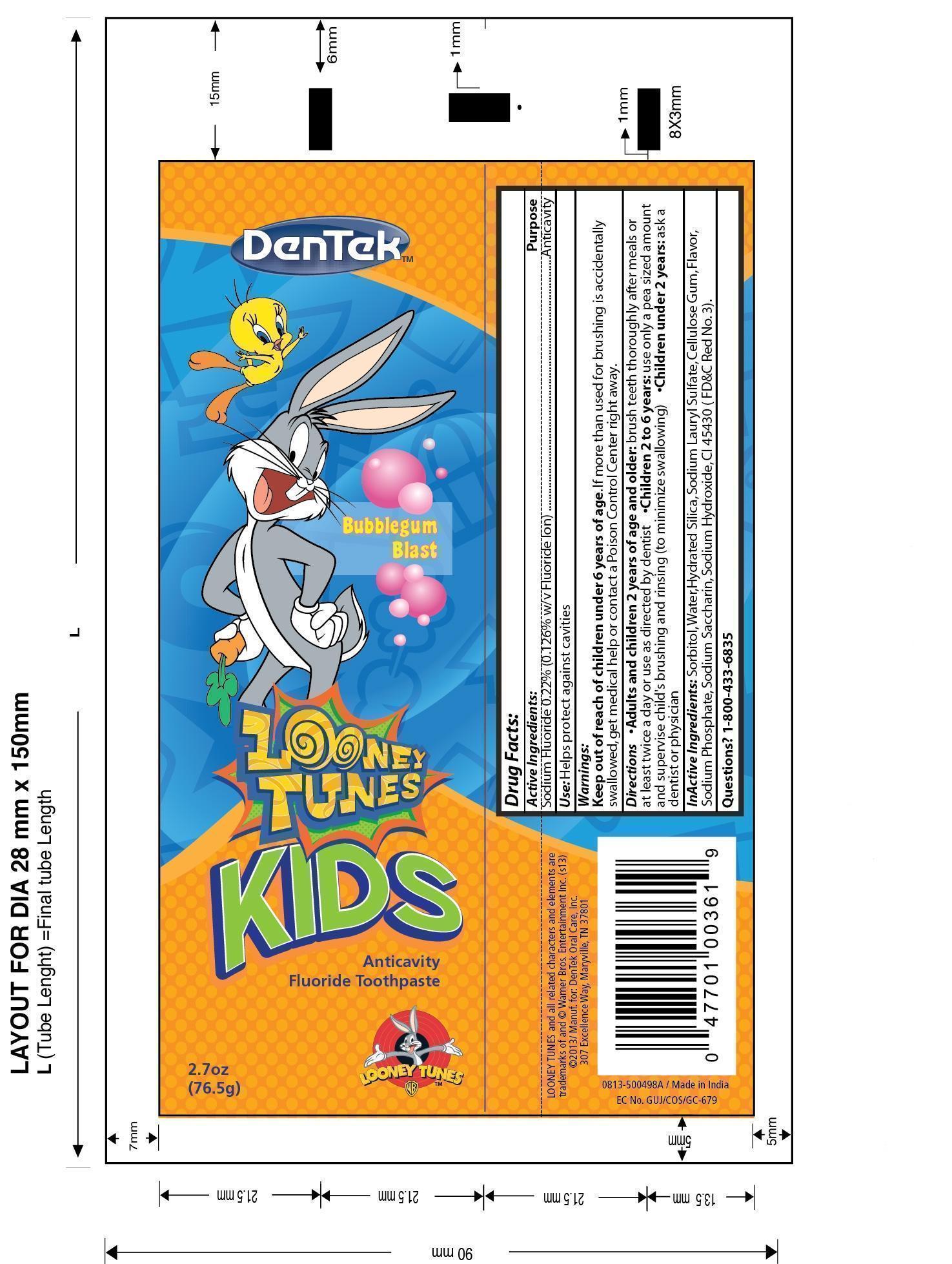 DRUG LABEL: DenTek Looney Tunes Kids
NDC: 60630-498 | Form: PASTE, DENTIFRICE
Manufacturer: DenTek Oral Care, Inc.
Category: otc | Type: HUMAN OTC DRUG LABEL
Date: 20160208

ACTIVE INGREDIENTS: SODIUM FLUORIDE 0.09639 g/76.5 g
INACTIVE INGREDIENTS: WATER 61.1618 g/76.5 g; HYDRATED SILICA 15.3 g/76.5 g; SODIUM PHOSPHATE 0.3825 g/76.5 g; SACCHARIN SODIUM 0.176 g/76.5 g; CARBOXYMETHYLCELLULOSE 0.918 g/76.5 g; ERYTHROSINE SODIUM ANHYDROUS 0.0008 g/76.5 g; SODIUM LAURYL SULFATE 1.3005 g/76.5 g; SODIUM HYDROXIDE 0.0765 g/76.5 g; SORBITOL 42.075 g/76.5 g

DenTek Looney Tunes Kids Anticavity Fluoride Toothpaste

Active Ingredients:

Sodium Fluoride 0.22% (0.126% w/v Fluoride Ion)

Purpose:

Anticavity

Use:

Helps protect against cavities

Warnings:

If more than used for brushing is accidentally swallowed, get medical help or contact a Poison Control Center right away.

Keep out of reach of children under 6 years of age.

DOSAGE AND ADMINISTRATION

Directions: . Adults and children 2 years of age and older: brush teeth thoroughly after meals or at least twice a day or use as directed by a dentist .Children 2 to 6 years: use only a pea sized amount and supervise child's brushing and rinsing (to minimize swallowing) .Children under 2 years: ask a dentist or physician

INACTIVE INGREDIENT

Inactive Ingredients: Sorbitol, Water, Hydrated Silica, Sodium Lauryl Sulfate, Cellulose Gum, Flavor, Sodium Phosphate, Sodium Saccharin, Sodium Hydroxide, CI 45430 (FD&C Red No. 3).

Questions? 1-800-433-6835